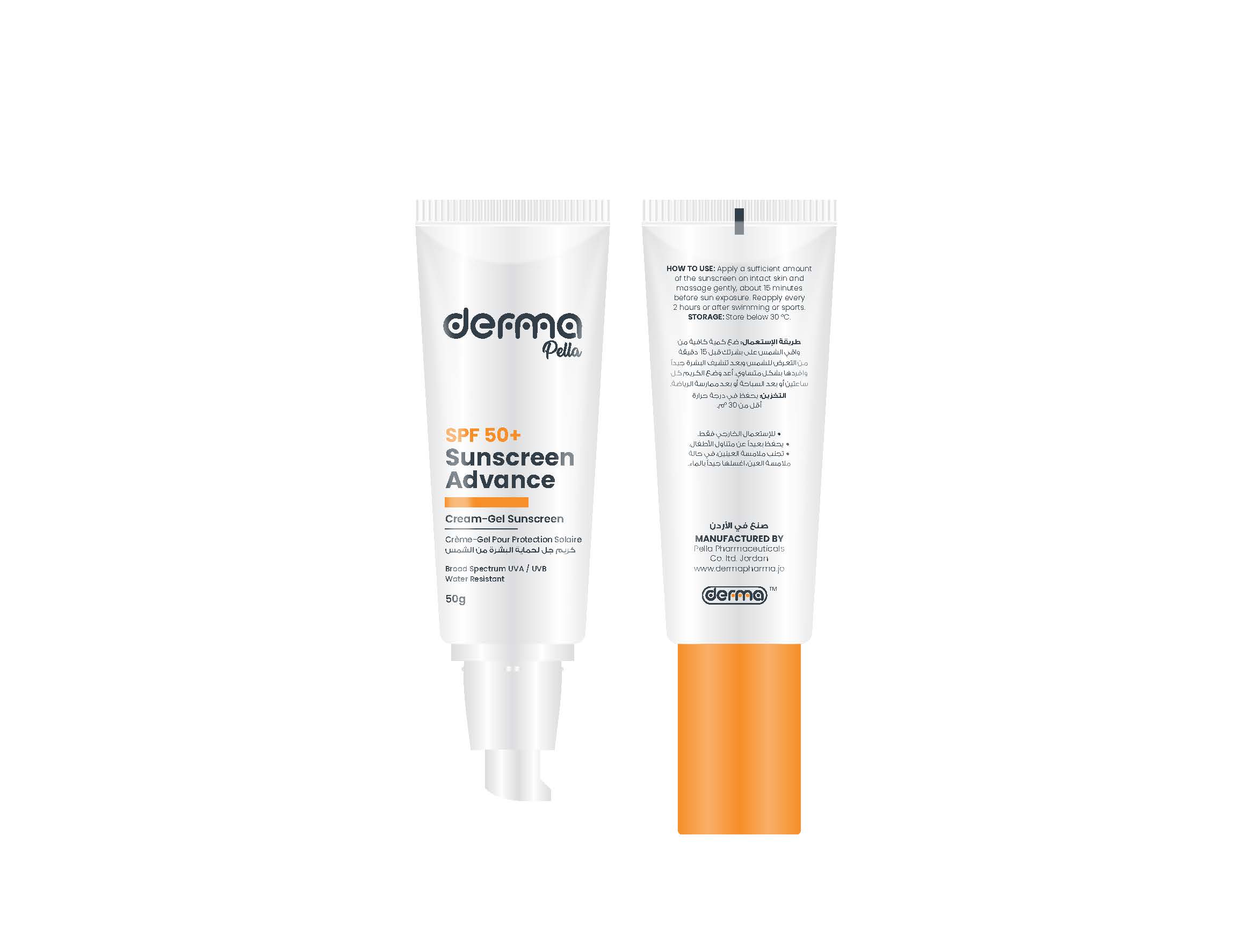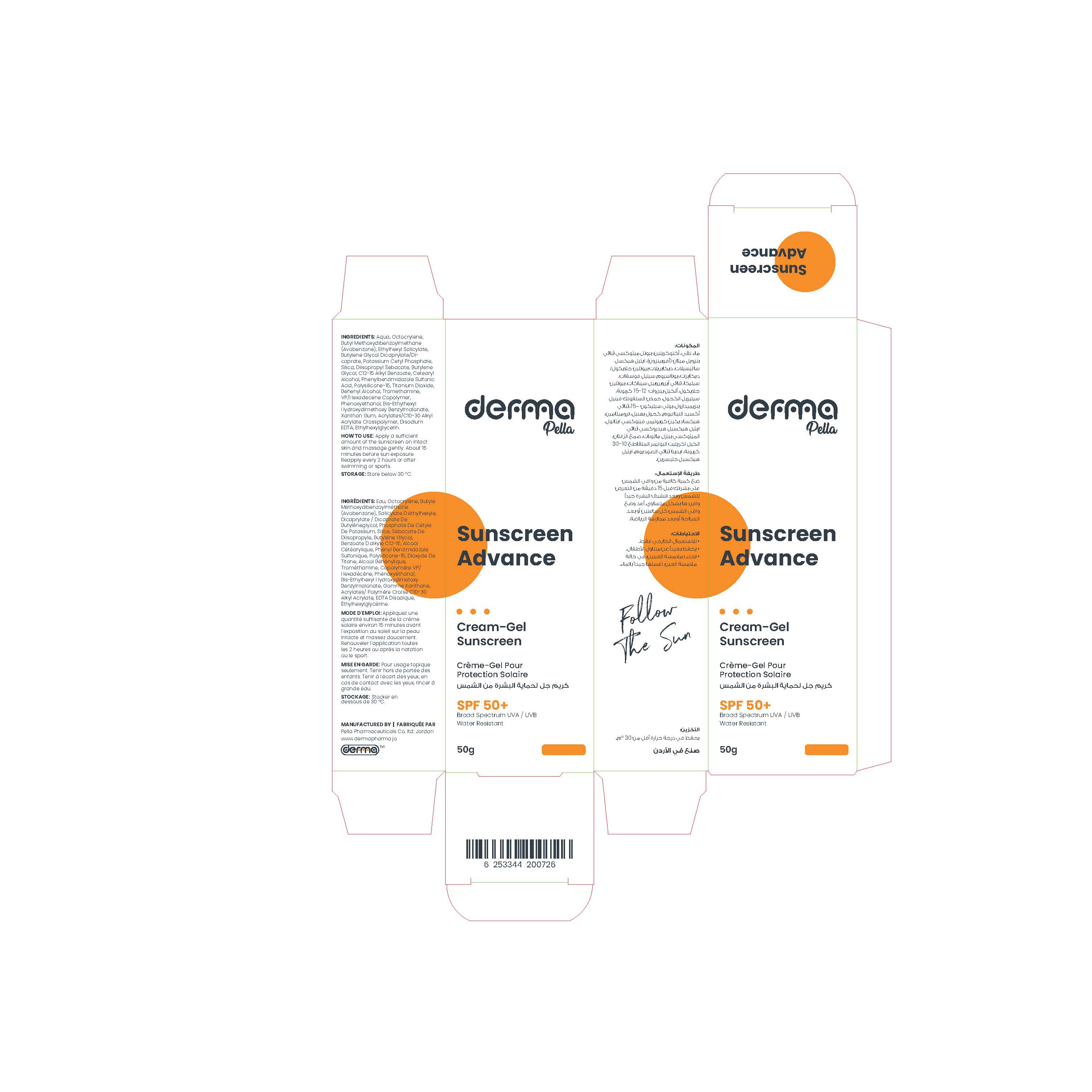 DRUG LABEL: Derma Pella Sunscreen Advance Cream-Gel
NDC: 82160-726 | Form: CREAM
Manufacturer: Pella Pharmaceuticals Co. Ltd
Category: otc | Type: HUMAN OTC DRUG LABEL
Date: 20250122

ACTIVE INGREDIENTS: ENSULIZOLE 20 mg/1 g; TITANIUM DIOXIDE 16 mg/1 g; OCTISALATE 50 mg/1 g; POLYSILICONE-15 20 mg/1 g; OCTOCRYLENE 100 mg/1 g; AVOBENZONE 50 mg/1 g
INACTIVE INGREDIENTS: WATER; CARBOMER COPOLYMER TYPE B (ALLYL PENTAERYTHRITOL CROSSLINKED); CETOSTEARYL ALCOHOL; EDETATE DISODIUM ANHYDROUS; POTASSIUM CETYL PHOSPHATE; DOCOSANOL; HEXADECYL POVIDONE; PHENOXYETHANOL; DIISOPROPYL SEBACATE; XANTHAN GUM; SILICON DIOXIDE; TROMETHAMINE; ETHYLHEXYLGLYCERIN; BIS-ETHYLHEXYL HYDROXYDIMETHOXY BENZYLMALONATE; BUTYLENE GLYCOL; ALKYL (C12-15) BENZOATE; BUTYLENE GLYCOL DICAPRYLATE/DICAPRATE

Sunscreen Advance

Form and Presentation

Cream-Gel: Plastic Tube, 50 g

Active Ingredients

Octocrylene, Butyl Methoxydibenzoylmethane (Avobenzone), Ethylhexyl Salicylate, Phenylbenzimidazole Sulfonic Acid, Polysilicone-15, Titanium Dioxide

Inactive Ingredients

Aqua, Butylene Glycol Dicaprylate/Dicaprate, Potassium Cetyl Phosphate, Silica, Diisopropyl Sebacate, Butylene Glycol, C12-15 Alkyl Benzoate, Cetearyl Alcohol, Behenyl Alcohol, Tromethamine, VP/Hexadecene Copolymer, Phenoxyethanol, Bis-Ethylhexyl Hydroxydimethoxy Benzylmalonate, Xanthan Gum, Acrylates/C10-30 Alkyl Acrylate Crosspolymer, Disodium EDTA, Ethylhexylglycerin

Purpose

Sunscreen

Properties

This product is developed to be suitable for all types of skin, with high sun protection factors (SPF 50 +) and optimum combination of UVB/UVA filters, they efficiently protect the skin pigmentation spots and skin ageing.

It is fast absorbing with dry touch and matte feel for optimal protection without leaving any white residue on skin.

Paraben Free, Water resistant.

Indications

Sunscreen for all skin types

Precautions

Keep out of reach of children

Warnings

- If irritation occurs, immediately rinse with water and discontinue use.
- If irritation persists, consult with a physician.
- Keep away from your eyes, in case of eye contact, flush with water.
- For external use only.

Contraindications

Hypersensitivity to any of the components.

Side Effects

There are no known side effects.

Dosage and Administration

Apply a sufficient amount of the sunscreen about 15 minutes before sun exposure on intact skin and massage gently. Reapply every 2 hours, after swimming, or sport.

Storage Conditions

Store below 30◦C.